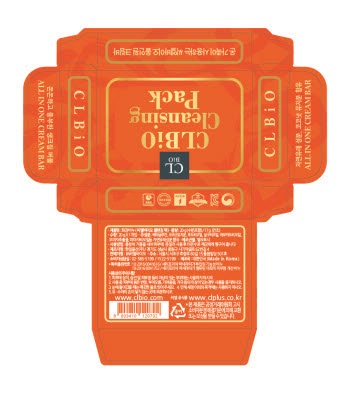 DRUG LABEL: CLBiO Cleansing Pack
NDC: 70874-0001 | Form: SOAP
Manufacturer: CLBiO Co., LTD.
Category: otc | Type: HUMAN OTC DRUG LABEL
Date: 20160825

ACTIVE INGREDIENTS: COCONUT OIL 91.9 g/100 g; GRAPE SEED OIL 0.3 g/100 g; APRICOT KERNEL OIL 0.3 g/100 g; AVOCADO OIL 0.3 g/100 g; SCHISANDRA CHINENSIS FRUIT 0.3 g/100 g; CASTOR OIL 0.3 g/100 g
INACTIVE INGREDIENTS: GLYCERIN

Drug Facts

ACTIVE INGREDIENT

SOAP BASE (COCONUT OIL), VITIS VINIFERA (GRAPE) SEED OIL, APRICOT KERNEL OIL, PERSEA GRATOSSIMA (AVOCADO) OIL, SCHIZANDRA CHINENSIS FRUIT EXTRACT, RICINUS COMMUNIS (CASTOR) SEED OIL.

INACTIVE INGREDIENT

CERIPORIA LACERATA FERMENT FILTRATE, GLYCERIN, ACORUS GRAMINEUS ROOT/STEM EXTRACT, ARTEMISIA VULGARIS EXTRACT, SOPHORA ANGUSTIFOLIA ROOT EXTRACT, SILKWORM EXTRACT, GINKGO BILOBA LEAF EXTRACT, MENTHA ARVENSIS LEAF EXTRACT, CNIDIUM OFFICINALE ROOT EXTRACT, LAVENDER

PURPOSE

SKIN PROTECTANT

KEEP OUT OF REACH OF THE CHILDREN

INDICATIONS AND USAGE

Apply soap to wet skin and rub, then rinse away with lukewarm water.

WARNINGS

1. Do not use in the following cases(Eczema and scalp wounds)
2.Side Effects
1)Due to the use of this druf if rash, irritation, itching and symptopms of hypersnesitivity occur dicontinue use and consult your phamacisr or doctor
3.General Precautions
1)If in contact with the eyes, wash out thoroughty with water If the symptoms are servere, seek medical advice immediately
2)This product is for exeternal use only. Do not use for internal use
4.Storage and handling precautions
1)If possible, avoid direct sunlight and store in cool and area of low humidity
2)In order to maintain the quality of the product and avoid misuse
3)Avoid placing the product near fire and store out in reach of children

DOSAGE AND ADMINISTRATION

for external use only